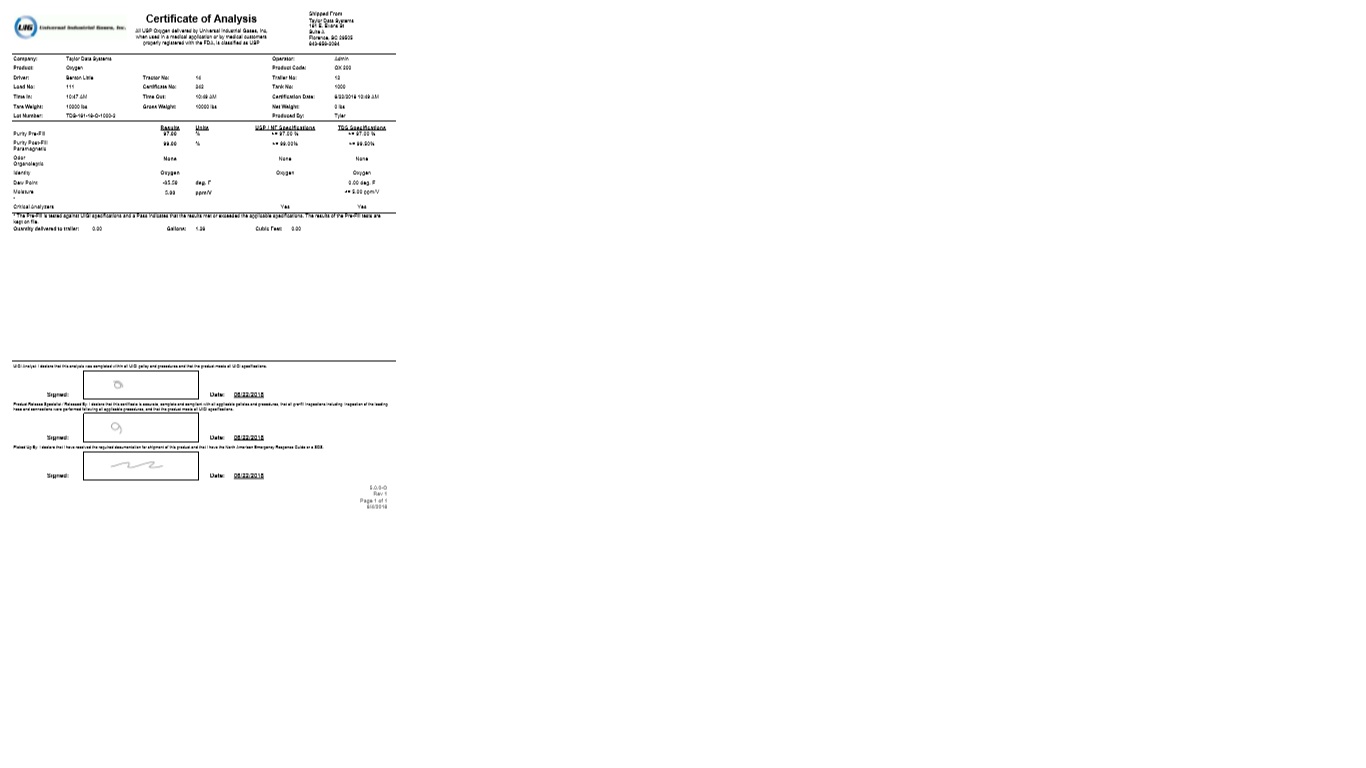 DRUG LABEL: Oxygen
NDC: 72457-003 | Form: GAS
Manufacturer: UCG Georgia, LLC
Category: prescription | Type: HUMAN PRESCRIPTION DRUG LABEL
Date: 20251216

ACTIVE INGREDIENTS: OXYGEN 990 mL/1 L

Oxygen

PACKAGE LABEL

UIG Universal Industrial Gases, Inc

Certificate of Analysis

All USP Oxygen delivered by Universal Industrial Gases, Inc, when used in a medical application or by medical customers properly registered with the FDA, is classified as USP

Shipped From

Taylor Data Systems

181 E. Evans St

Suite A

Florence, SC 29505

843-656-2084

Company: Taylor Data Systems Operator: Admin

Product: Oxygen Product Code: OX 200

Driver: Benton Little Tractor No: 14 Trailer No: 12

Load No: 111 Certificate No: 242 Tank No: 1000

Time In: 10:47 AM Time Out: 10:49 AM Certification Date: 6/22/2018 10:49 AM

Tare Weight: 10000 lbs Gross Weight: 10000 lbs Net Weight: 0 lbs

Lot Number: TDS-161-18-O-1000-2 Produced by: Tyler

Results Units USP/NF Specifications TDS Specifications

Purity Pre-Fill 97.00 % >=97.00 % >=97.00 %

Purity Post-Fill 99.00 $ >=99.00 % >=99.50 %

Paramagnetic

Odor None None None

Organoleptic

Identity Oxygen Oxygen Oxygen

Dew Point -85.50 deg. F 0.00 deg. F

Moisture 5.00 ppm/V <=5.00 ppm/V

-

Critical Analyzers Yes Yes

*The Pre-Fill is tested against UIGI specifications and a Pass indicates that the results met or exceeded the applicable specifications. The results of the Pre-Fill tests are kept on file.

Quantity delivered to trailer: 0.00 Gallons: 1.26 Cubic Feet: 0.00

UIGI Analyst: I declare that this analysis was completed within all UIGI policy and procedures and that the product meets all UIGI specifications.

Signed: Date: 06/22/2018

Product Release Specialist / Released By: I declare that this certificate is accurate, complete and compliant with all applicable policies and procedures, that all pre-fill inspections including inspection of the loading hose and connections were performed following all applicable procedures, and that the product meets all UIGI specifications.

Signed: Date: 06/22/2018

Picked Up By: I declare that I have received the required documentation for shipment of this product and that I have the North American Emergency Response Guide or a SDS.

Signed: Date: 06/22/2018